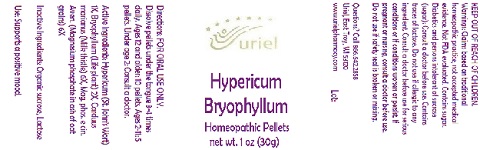 DRUG LABEL: Hypericum Bryophyllum
NDC: 48951-5061 | Form: PELLET
Manufacturer: Uriel Pharmacy Inc.
Category: homeopathic | Type: HUMAN OTC DRUG LABEL
Date: 20180515

ACTIVE INGREDIENTS: ST. JOHN'S WORT 1 [hp_X]/1 1; KALANCHOE DAIGREMONTIANA LEAF 2 [hp_X]/1 1; MILK THISTLE 6 [hp_X]/1 1; MAGNESIUM PHOSPHATE, TRIBASIC, PENTAHYDRATE 6 [hp_X]/1 1
INACTIVE INGREDIENTS: SUCROSE

Hypericum Bryophyllum

INDICATIONS AND USAGE

Directions: FOR ORAL USE ONLY.

DOSAGE AND ADMINISTRATION

Dissolve pellets under the tongue 3-4
times daily. Ages 12 and older: 10 pellets.
Ages 2-11: 5 pellets. Under age 2: Consult
a doctor.

ACTIVE INGREDIENT

Active Ingredients: Hypericum (St. John’s Wort) 1X, Bryophyllum (Life plant) 2X, Carduus marianus (Milk thistle) 6X, Mag. phos. e cin. Aven. (Magnesium phosphate in ash of oat grains) 6X

Inactive Ingredients: Sucrose, Lactose

PURPOSE

Use: Supports a positive mood.

KEEP OUT OF REACH OF CHILDREN.

WARNINGS

Warnings: Claims based on traditional homeopathic practice, not accepted medical evidence. Not FDA evaluated. Contains sugar. Diabetics and persons intolerant of sucrose (sugar): Consult a doctor before use. Contains traces of lactose. Do not use if allergic to any ingredient. Consult a doctor before use for serious conditions or if conditions worsen or persist. If pregnant or nursing, consult a doctor before use. Do not use if safety seal is broken or missing.

Questions? Call 866.642.2858
Uriel, East Troy, WI 53120
www.urielpharmacy.com